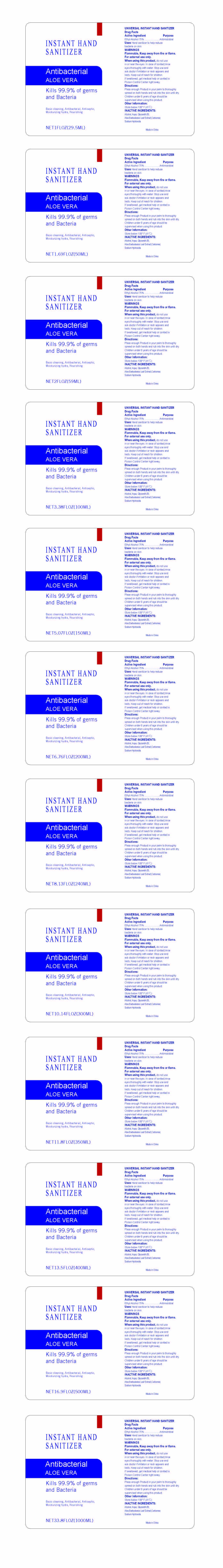 DRUG LABEL: INSTANT HAND SANITIZER
NDC: 74657-001 | Form: GEL
Manufacturer: Double Body Biotech Limited
Category: otc | Type: HUMAN OTC DRUG LABEL
Date: 20200407

ACTIVE INGREDIENTS: ALCOHOL 75 mL/100 mL
INACTIVE INGREDIENTS: GLYCERETH-26; CARBOMER HOMOPOLYMER, UNSPECIFIED TYPE; SODIUM HYDROXIDE; WATER; ALOE VERA LEAF

Active Ingredient

Ethyl Alcohol 75%

Purpose

Antimicrobial

Uses

Hand sanitizer to help reduce bacteria on skin.

WARNINGS

Flammable, Keep away from fire or flame.
For external use only.

When using this product

do not use in or near the eyes. In case of contact,rinse eyes thoroughly with water. Stop use and
ask doctor if irritation or rash appears and lasts. Keep out of reach for children. If swallowed, get

medical help or contact a Poison Control Center right away.

Directions

Place enough Product in your palm to thoroughly spread on both hands and rub into the skin until dry.
Children under 6 years of age should be supervised when using this product.

Other Information

Store below 106° F.(41℃)

INACTIVE INGREDIENTS

Alcohol, Aqua, Glycereth-26, Aloe Barbadensis Leaf Extract,Carbomer,Sodium Hydroxide.